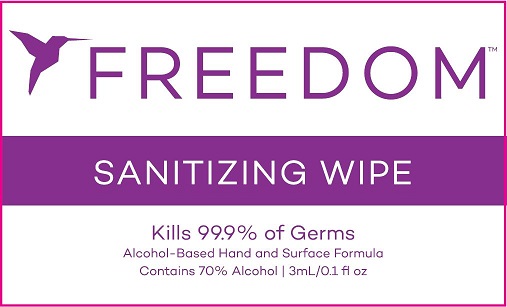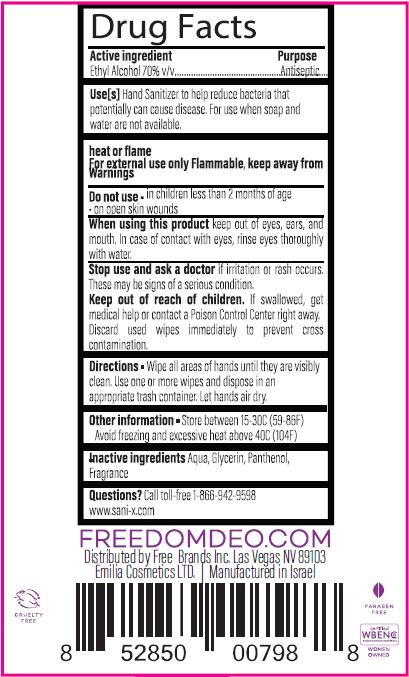 DRUG LABEL: SANITIZING WIPES
NDC: 43219-101 | Form: SOLUTION
Manufacturer: Emilia Cosmetics Ltd
Category: otc | Type: HUMAN OTC DRUG LABEL
Date: 20201129

ACTIVE INGREDIENTS: ALCOHOL 70 mL/100 mL
INACTIVE INGREDIENTS: WATER; GLYCERIN; PANTHENOL

SANITIZING WIPES

ACTIVE INGREDIENT

ETHYL ALCOHOL 70% V/V

PURPOSE

ANTISEPTIC

USES

HAND SANITIZER TO HELP REDUCE BACTERIA THAT POTENTIALLY CAN CAUSE DISEASE. FOR USE WHEN SOAP AND WATER ARE NOT AVAILABLE.

WARNINGS

FOR EXTERNAL USE ONLY.

FLAMMABLE, KEEP AWAY FROM HEAT OR FLAME.

DO NOT USE

- IN CHILDREN LESS THAN 2 MONTHS OF AGE
- ON OPEN SKIN WOUNDS

WHEN USING THIS PRODUCT KEEP OUT OF EYES, EARS, AND MOUTH. IN CASE OF CONTACT WITH EYES, RINSE EYES THOROUGHLY WITH WATER.

STOP USE AND ASK A DOCTOR IF IRRITATION OR RASH OCCURS. THESE MAY BE SIGNS OF A SERIOUS CONDITION.

KEEP OUT OF REACH OF CHILDREN. IF SWALLOWED, GET MEDICAL HELP OR CONTACT A POISON CONTROL CENTER RIGHT AWAY.

OTHER SAFETY INFORMATION

DISCARD USED WIPES IMMEDIATELY TO PREVENT CROSS CONTAMINATION.

DIRECTIONS

- WIPE ALL AREAS OF HANDS UNTIL THEY ARE VISIBLY CLEAN. USE ONE OR MORE WIPES AND DISPOSE IN AN APPROPRIATE TRASH CONTAINER. LET HANDS AIR DRY.

OTHER INFORMATION

- STORE BETWEEN 15-30C (59-86F)
- AVOID FREEZING AND EXCESSIVE HEAT ABOVE 40C (104F)

INACTIVE INGREDIENTS

AQUA, GLYCERIN, PANTHENOL, FRAGRANCE.

QUESTIONS?

CALL TOLL-FREE 1-866-942-9598 OR VISIT WWW.SANI-X.COM